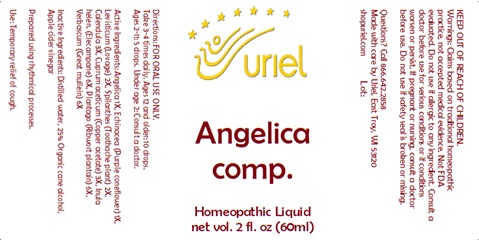 DRUG LABEL: Angelica Comp.
NDC: 48951-1035 | Form: LIQUID
Manufacturer: Uriel Pharmacy Inc.
Category: homeopathic | Type: HUMAN OTC DRUG LABEL
Date: 20241126

ACTIVE INGREDIENTS: CUPRIC ACETATE 3 [hp_X]/1 mL; INULA HELENIUM ROOT 6 [hp_X]/1 mL; PLANTAGO MAJOR LEAF 6 [hp_X]/1 mL; VERBASCUM DENSIFLORUM LEAF 6 [hp_X]/1 mL; CALENDULA OFFICINALIS FLOWERING TOP 3 [hp_X]/1 mL; ANGELICA ARCHANGELICA ROOT 1 [hp_X]/1 mL; ECHINACEA ANGUSTIFOLIA 1 [hp_X]/1 mL; LEVISTICUM OFFICINALE ROOT 2 [hp_X]/1 mL; ACMELLA OLERACEA WHOLE 2 [hp_X]/1 mL
INACTIVE INGREDIENTS: WATER; SODIUM CHLORIDE; APPLE CIDER VINEGAR

Angelica Comp.

INDICATIONS AND USAGE

Directions: FOR ORAL USE ONLY.

DOSAGE AND ADMINISTRATION

Take 3-4 times daily. Ages 12 and older: 10 drops. Ages 2-11: 5 drops. Under age 2: Consult a doctor.

ACTIVE INGREDIENT

Active Ingredients: Angelica 1X, Echinacea (Purple coneflower) 1X, Levisticum (Lovage) 2X, Spilanthes (Toothache plant) 2X, Calendula 3X, Cuprum aceticum (Copper acetate) 3X, Inula helen. (Elecampane) 6X, Plantago (Ribwort plantain) 6X, Verbascum (Great mullein) 6X

INACTIVE INGREDIENT

Inactive Ingredients: Distilled water, 20% Organic cane alcohol, Organic apple cider vinegar

Prepared using rhythmical processes.

PURPOSE

Use: Temporary relief of cough.

KEEP OUT OF REACH OF CHILDREN.

WARNINGS

Warnings: Claims based on traditional homeopathic practice, not accepted medical evidence. Not FDA evaluated. Do not use if allergic to any ingredient. Consult a doctor before use for serious conditions or if conditions worsen or persist. If pregnant or nursing, consult a doctor before use. Do not use if safety seal is broken or missing.

QUESTIONS

Questions? Call 866.642.2858 Made with care by Uriel, East Troy, WI 53120 shopuriel.com Lot: